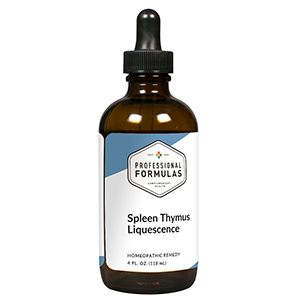 DRUG LABEL: Spleen Thymus Liquescence
NDC: 63083-3023 | Form: LIQUID
Manufacturer: Professional Complementary Health Formulas
Category: homeopathic | Type: HUMAN OTC DRUG LABEL
Date: 20190815

ACTIVE INGREDIENTS: HELIANTHUS ANNUUS FLOWERING TOP 2 [hp_X]/118 mL; ECHINACEA ANGUSTIFOLIA WHOLE 3 [hp_X]/118 mL; QUERCUS ALBA BARK 3 [hp_X]/118 mL; CINCHONA OFFICINALIS BARK 4 [hp_X]/118 mL; SODIUM CHLORIDE 6 [hp_X]/118 mL; CEANOTHUS AMERICANUS LEAF 6 [hp_X]/118 mL; QUININE ARSENITE 6 [hp_X]/118 mL; BOS TAURUS SPLEEN 6 [hp_X]/118 mL; HYSSOPUS OFFICINALIS WHOLE 6 [hp_X]/118 mL
INACTIVE INGREDIENTS: ALCOHOL; WATER

T23

ACTIVE INGREDIENTS

Helianthus annuus 2X
Echinacea angustifolia 3X
Quercus glandium 3X
Cinchona officinalis 4X
Aqua marina 6X
Ceanothus americanus 6X
Chininum arsenicosum 6X
Spleen 6X
Thymus 6X
Natrum muriaticum 12X

QUESTIONS

Professional Formulas

PO Box 2034 Lake Oswego, OR 97035

INDICATIONS

For the temporary relief of mild pain in the abdomen or shoulder.*

PURPOSE

*Claims based on traditional homeopathic practice, not accepted medical evidence. Not FDA evaluated.

WARNINGS

Severe or persistent symptoms may be serious. Consult a doctor promptly. Keep out of the reach of children. In case of overdose, get medical help or contact a poison control center right away. If pregnant or breastfeeding, ask a healthcare professional before use.

Keep out of the reach of children.

PREGNANCY OR BREAST FEEDING

If pregnant or breastfeeding, ask a healthcare professional before use.

DIRECTIONS

Place drops under tongue 30 minutes before/after meals. Adults and children 12 years and over: Take one full dropper up to 2 times per day. Consult a physician for use in children under 12 years of age.

OTHER INFORMATION

Tamper resistant. If seal is broken, do not use. After opening, close container tightly and store at room temperature away from heat.

INACTIVE INGREDIENTS

20% ethanol, purified water.

LABEL

Est 1985

Professional Formulas

Complementary Health

Spleen Thymus Liquescence

Homeopathic Remedy

4 FL. OZ. (118 mL)